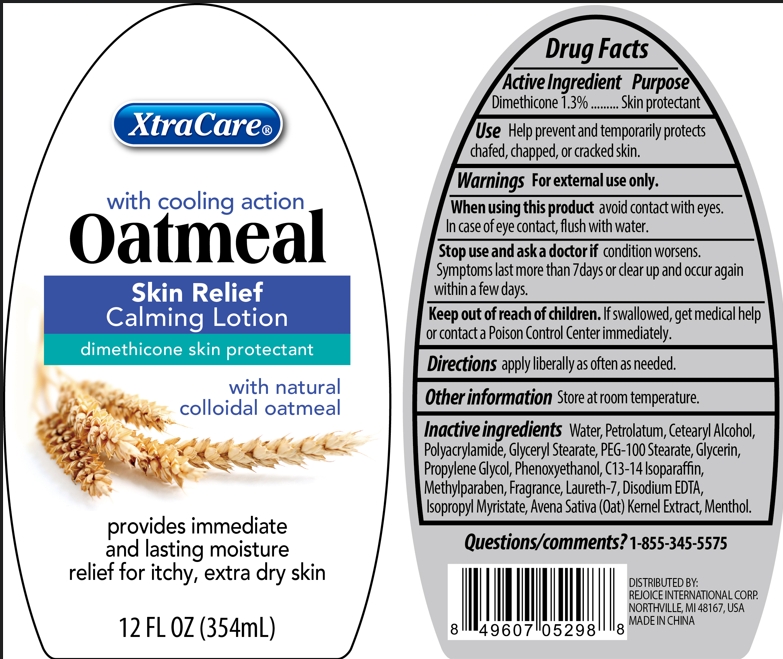 DRUG LABEL: XtraCare with cooling action Oatmeal Skin Relief Calmin
NDC: 57337-038 | Form: LOTION
Manufacturer: Rejoice International
Category: otc | Type: HUMAN OTC DRUG LABEL
Date: 20250209

ACTIVE INGREDIENTS: DIMETHICONE 5 mg/354 mg
INACTIVE INGREDIENTS: MINERAL OIL; ISOPROPYL MYRISTATE; GLYCERIN; GLYCERYL MONOSTEARATE; PROPYLENE GLYCOL; PEG-100 STEARATE; POLYACRYLAMIDE (1500 MW); CETYL ALCOHOL; OAT; DMDM HYDANTOIN; STEARYL ALCOHOL; C13-14 ISOPARAFFIN; LAURETH-7; EDETATE DISODIUM; MENTHOL; ALOE VERA LEAF; METHYLPARABEN; PROPYLPARABEN; WATER

XtraCare with cooling action Oatmeal Skin Relief Calmin

Active Ingredient Purpose

Dimethicone 1/3% ......... Skin Protectant

PURPOSE

XtraCare (with cooling action) Oatmeal Skin Relief Calming Lotion

dimethicone skin protectant

with natural colloidal oatmeal

provides immediate and lasting moisture relief for itchy, extra dry skin

12 fl oz (354 mL)

Keep out of reach of children. If swallowed, get medical help or contact a Poison Control Center immediately.

INDICATIONS AND USAGE

Use Help prevent and temporarily protects chafed, chapped, or cracked skin.

Warnings For external use only.

When using this product avoid contact with eyes. In case of eye contact, flush with water.

Stop use and ask a doctor if condition worsens. Symptoms last more than 7 days or clear up and occur again within a few days.

DOSAGE AND ADMINISTRATION

Directions apply liberally as often as needed.

Other Information store at room temperature.

DISTRIBUTED BY:

REJOICE INTERNATIONAL INC.

48325 BINGHAMPTON DR.,

NORTHVILLE, MI 48168 USA

MADE IN CHINA

Inactive Ingredients

water, paraffinum liquidum, isopropyl myristate, glycerin, glyceryl stearate, propylene glycol, PEG-100 stearate, polyacrylamide, cetyl alcohol, avena sativa kernel extract, fragrance, DMDM hydantoin, stearyl alcohol, c13-14 isoparaffin, laureth-7, disodium EDTA, menthol, aloe barbadensis leaf juice, methylparaben, propylparaben.